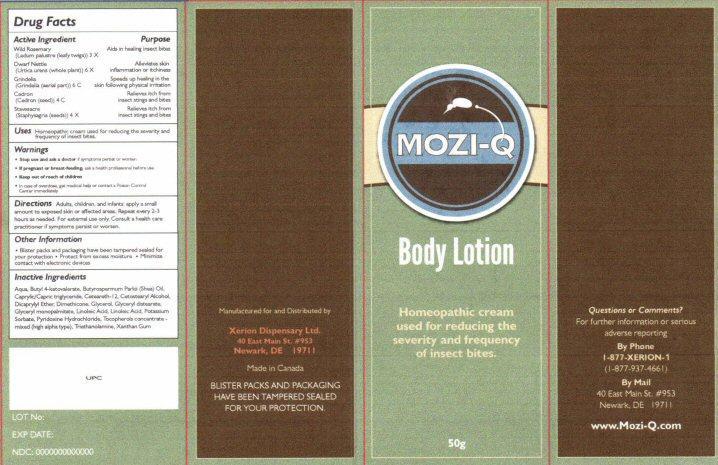 DRUG LABEL: MOZI-Q
NDC: 53590-104 | Form: LOTION
Manufacturer: Xerion Dispensary Ltd.
Category: homeopathic | Type: HUMAN OTC DRUG LABEL
Date: 20231217

ACTIVE INGREDIENTS: LEDUM PALUSTRE TWIG 3 [hp_X]/50 g; URTICA URENS 6 [hp_X]/50 g; GRINDELIA HIRSUTULA FLOWERING TOP 6 [hp_C]/50 g; SIMABA CEDRON SEED 4 [hp_C]/50 g; DELPHINIUM STAPHISAGRIA SEED 4 [hp_X]/50 g
INACTIVE INGREDIENTS: WATER; BUTYL LEVULINATE; SHEANUT OIL; MEDIUM-CHAIN TRIGLYCERIDES; CETEARETH-12; CETOSTEARYL ALCOHOL; DICAPRYLYL ETHER; DIMETHICONE; GLYCERIN; GLYCERYL DISTEARATE; GLYCERYL PALMITATE; LINOLEIC ACID; POTASSIUM SORBATE; PYRIDOXINE HYDROCHLORIDE; TOCOPHEROL; TROLAMINE; XANTHAN GUM

Drug Facts Active Ingredients

Wild Rosemary (Ledum palustre (leafy twigs)) 3 X
Dwarf Nettle (Urtica urens (whole plant)) 6 X
Grindelia (Grindelia (aerial part)) 6 C
Cedron (Cedron (seed)) 4 C
Stavesacre (Staphysagria (seeds)) 4 X

Purpose

Aids in healing insect bites
Alleviates skin inflammation or itchiness
Speeds up healing in the skin following physical irritation
Relieves itch from insect stings and bites

Keep out of reach of children

Uses

Homeopathic cream used for reducing the severity and frequency of insect bites.

Warnings

- Stop use and ask a doctor if symptoms persist or worsen
- If pregnant or breast-feeding, ask a health professional before use.
- In case of overdose, get medical help or contact a Poison Control Center immediately.

Directions

Adults, children,and infants: apply a small amount to exposed skin or affected areas, Repeat every 2-3 hours as needed. for external use only. Consult a health care practitioner if symptoms persist or worsen.

Other Information

- Blister packs and packaging have been tampered sealed for your protection
- Protect from excessive moisture
- Minimize contact with electronic devices

Inactive Ingredients

Aqua, Butyl 4-ketovalerate, Butyrospermum Parkii (Shea) Oil, Caprylic/Capric triglycerides, Ceteareth-12, Cetostearyl Alcohol, Dicaprylyl Ether, Glycerol, Glyceryl distearate, Glyceryl monopalmitate, Linoleic Acid, Potassium Sorbate, Pyridoxine Hydrochloride, Tocopherols concentrate mixed (high alpha type), Triethanolamine, Xanthan Gum

Product label

MOZI-Q

Body Lotion

Homeopathic cream used for the reducing the severity and frequency of insect bites.

50g

Questions or Comments?

For further information or serious adverse reporting

By Phone 1-877-XERION-1 (1-877-937-4661)

By Mail 40 East Main St. #953 Newark, DE 19711

www.Mozi-Q.com

Manufactured for and Distributed by

Xerion Dispensary Ltd.

40 East Main St. #953

Newark, DE 19711

Made in Canada

BLISTER PACKS AND PACKAGING HAVE BEEN TAMPERED SEALED FOR YOUR PROTECION

UPC

LOT No

EXP DATE

NDC 0000000000000